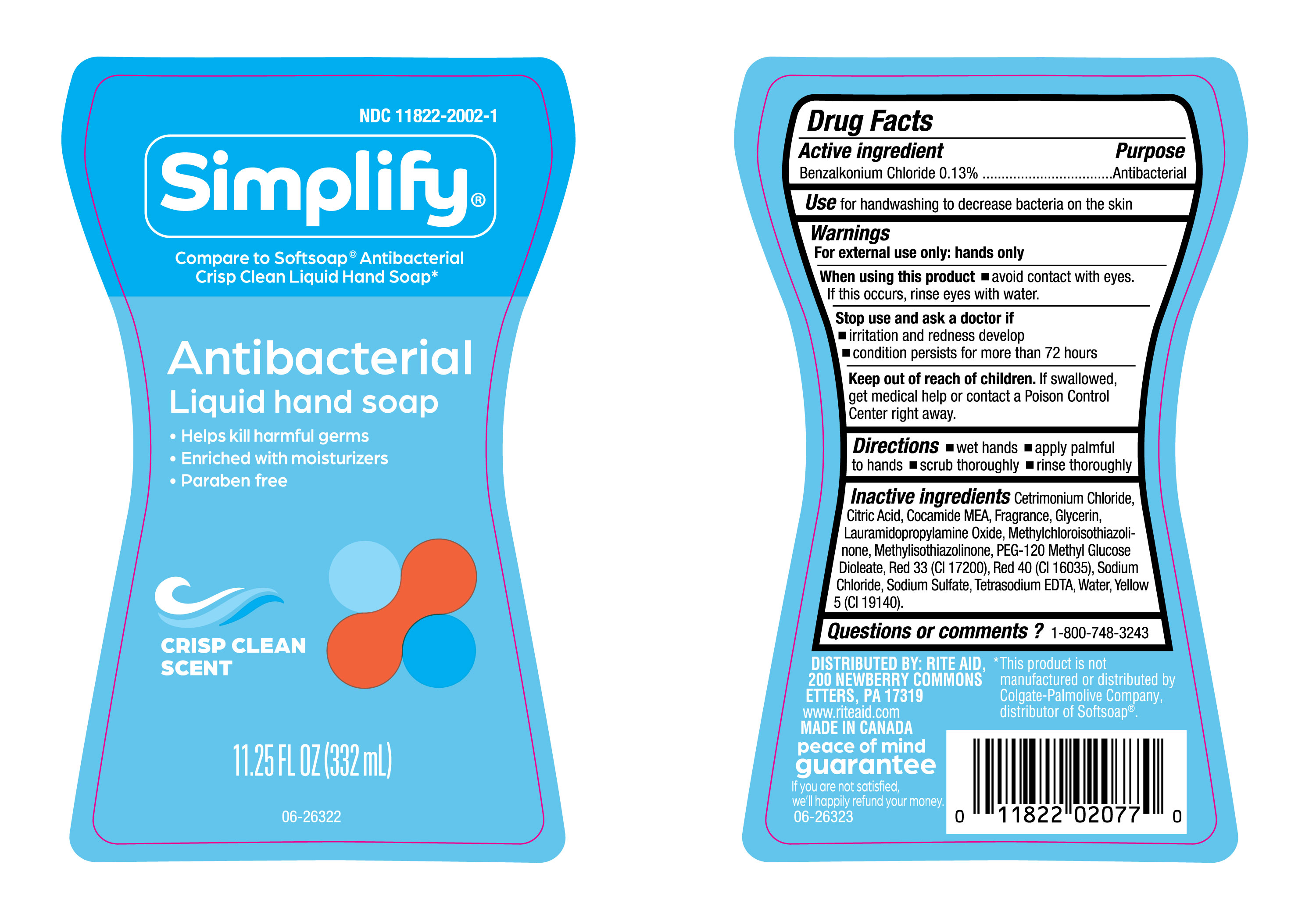 DRUG LABEL: Simplify Crisp Clean LHS
NDC: 11822-2002 | Form: LIQUID
Manufacturer: RITE AID CORPORATION
Category: otc | Type: HUMAN OTC DRUG LABEL
Date: 20250116

ACTIVE INGREDIENTS: BENZALKONIUM CHLORIDE 130 mg/100 mL
INACTIVE INGREDIENTS: RED 33; METHYLISOTHIAZOLINONE; CITRIC ACID; GLYCERIN; LAURAMIDOPROPYLAMINE OXIDE; SODIUM SULFATE; FRAGRANCE CLEAN ORC0600327; YELLOW 5; CETRIMONIUM CHLORIDE; COCAMIDE MEA; METHYLCHLOROISOTHIAZOLINONE; PEG-120 METHYL GLUCOSE DIOLEATE; RED 40; WATER; SODIUM CHLORIDE; TETRASODIUM EDTA

NDC-11822-2002-1, Simplify- Crisp Clean Scent

Active Ingredient

Benzalkonium Chloride 0.13%

Purpose

Antbacterial

Uses

For handwashing to decrease bacteria on the skin.

Warnings

For external use only: hands only.

When using this product

- Avoid contact with eyes. If this occurs, rinse eyes with water.

Stop use and ask a doctor if

- Irritation andredness develop
- Condition persists for more that 72 hours.

Keep out of reach of Children

If swallowed, get medical help or contact a Poison Control Center right away.

Directions

- Wet Hands.
- Apply palmful to hands.
- Scrub thoroughly.
- rinse thoroughly.

Inactive Ingredients

Cetrimonium Chloride, Citric Acid, Cocamide MEA, Fragrance, Glycerin, Lauramidopropylamine Oxide, Methylchloroisothiazolinone, Methylisothiazolinone, PEG-120 Methyl Glucose Dioleate, Red 33 (CI17200), Red 40 (CI16035), Sodum Chloride, Sodium Sulfate, Tetrasodium EDTA, Water, Yellow 5 (CI 19140).

Questions or comments?

1-800-748-3243.